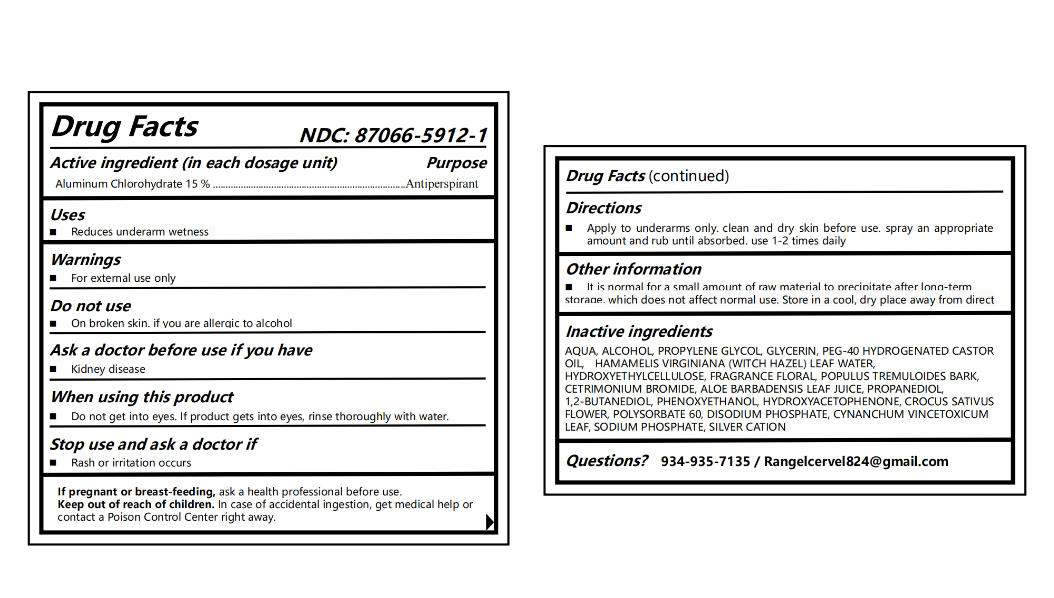 DRUG LABEL: 87066-5912
NDC: 87066-5912 | Form: SPRAY
Manufacturer: Hubei Redrui Building Materials Co., Ltd.
Category: otc | Type: HUMAN OTC DRUG LABEL
Date: 20250912

ACTIVE INGREDIENTS: ALUMINUM CHLOROHYDRATE 15 g/100 g
INACTIVE INGREDIENTS: CYNANCHUM VINCETOXICUM LEAF 0.01 g/100 g; HAMAMELIS VIRGINIANA (WITCH HAZEL) LEAF WATER 0.5 g/100 g; HYDROXYETHYLCELLULOSE 0.6 g/100 g; HYDROXYACETOPHENONE 0.255 g/100 g; ALCOHOL 10 g/100 g; PROPANEDIOL 0.5125 g/100 g; AQUA 65.9719 g/100 g; POLYSORBATE 60 0.1 g/100 g; PHENOXYETHANOL 0.3 g/100 g; PEG-40 HYDROGENATED CASTOR OIL 0.55 g/100 g; FRAGRANCE FLORAL ORC0902236 0.1 g/100 g; GLYCERIN 2 g/100 g; SILVER CATION 0.0001 g/100 g; ALOE BARBADENSIS LEAF JUICE 0.1 g/100 g; SODIUM PHOSPHATE 0.01 g/100 g; DISODIUM PHOSPHATE 0.05 g/100 g; POPULUS TREMULOIDES BARK 0.2 g/100 g; CETRIMONIUM BROMIDE 0.03 g/100 g; PROPYLENE GLYCOL 3.155 g/100 g; 1,2-BUTANEDIOL 0.5 g/100 g; CROCUS SATIVUS FLOWER 0.0555 g/100 g

Active ingredient

Aluminum Chlorohydrate 15%

Purpose

Antiperspirant

Uses

- Reduces underarm wetness

Warnings

- For external use only

Do not use

- On broken skin. if you are allergic to alcohol

Ask a doctor before use if you have

- Kidney disease

When using this product

- Do not get into eyes. If product gets into eyes, rinse thoroughly with water.

Stop use and ask a doctor if

- Rash or irritation occurs

Pregnancy or breast feeding section

If pregnant or breast-feeding, ask a health professional before use.

Keep out of reach of children

In case of accidental ingestion, get medical help or contact a Poison Control Center right away.

Directions

- Apply to underarms only. clean and dry skin before use. spray an appropriate amount and rub until absorbed. use 1-2 times daily

Other information

- It is normal for a small amount of raw material to precipitate after long-term storage, which does not affect normal use. Store in a cool, dry place away from direct

Inactive ingredients

AQUA, ALCOHOL, PROPYLENE GLYCOL, GLYCERIN, PEG-40 HYDROGENATED CASTOR OIL, HAMAMELIS VIRGINIANA (WITCH HAZEL) LEAF WATER, HYDROXYETHYLCELLULOSE, FRAGRANCE FLORAL, POPULUS TREMULOIDES BARK, CETRIMONIUM BROMIDE, ALOE BARBADENSIS LEAF JUICE, PROPANEDIOL, 1,2-BUTANEDIOL, PHENOXYETHANOL, HYDROXYACETOPHENONE, CROCUS SATIVUS FLOWER, POLYSORBATE 60, DISODIUM PHOSPHATE, CYNANCHUM VINCETOXICUM LEAF, SODIUM PHOSPHATE, SILVER CATION

Questions or comments?

934-935-7135 / Rangelcervel824@gmail.com

Box Front Panel

ELIMINATE BODY ODOR. (Eliminate Body Odor. Reduce Body Odor.) (The spring breeze for ten miles is not as good as you, fortunately Xinting found you.)